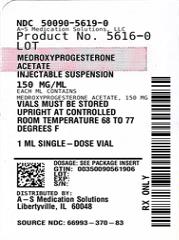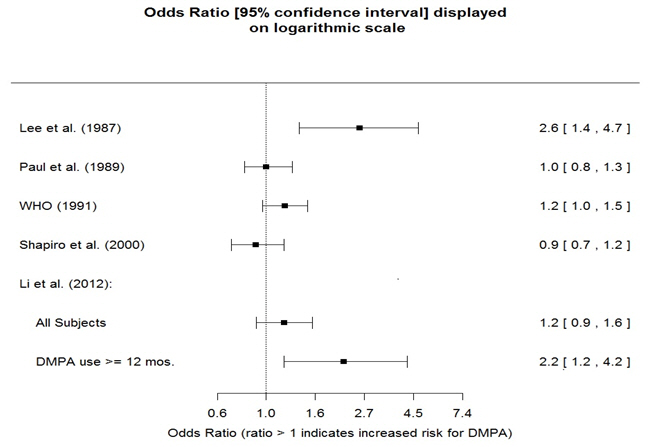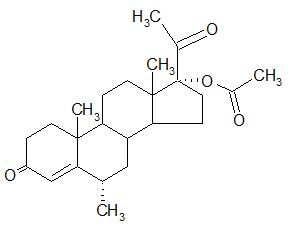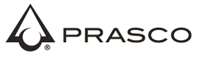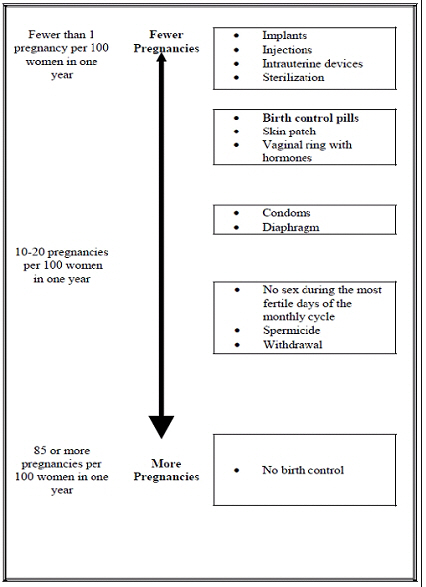 DRUG LABEL: medroxyprogesterone acetate
NDC: 50090-5619 | Form: INJECTION, SUSPENSION
Manufacturer: A-S Medication Solutions
Category: prescription | Type: HUMAN PRESCRIPTION DRUG LABEL
Date: 20260223

ACTIVE INGREDIENTS: MEDROXYPROGESTERONE ACETATE 150 mg/1 mL
INACTIVE INGREDIENTS: POLYETHYLENE GLYCOL 3350 28.9 mg/1 mL; POLYSORBATE 80 2.41 mg/1 mL; SODIUM CHLORIDE 8.68 mg/1 mL; METHYLPARABEN 1.37 mg/1 mL; PROPYLPARABEN 0.15 mg/1 mL; AQUA; SODIUM HYDROXIDE; HYDROCHLORIC ACID

HIGHLIGHTS OF PRESCRIBING INFORMATION

These highlights do not include all the information needed to use MEDROXYPROGESTERONE ACETATE (MPA) Injectable Suspension, USP safely and effectively. See full prescribing information for MPA INJECTABLE SUSPENSION, USP.
MEDROXYPROGESTERONE ACETATE (MPA) Injectable Suspension, USP, for intramuscular use
Initial U.S. Approval: 1959

WARNING: LOSS OF BONE MINERAL DENSITY

See full prescribing information for complete boxed warning.

- Women who use Medroxyprogesterone Acetate (MPA) Injectable Suspension, USP may lose significant bone mineral density. Bone loss is greater with increasing duration of use and may not be completely reversible. (5.1)
- It is unknown if use of MPA Injectable Suspension, USP during adolescence or early adulthood, a critical period of bone accretion, will reduce peak bone mass and increase the risk for osteoporotic fracture in later life. (5.1)
- MPA Injectable Suspension, USP is not recommended as a long-term (i.e., longer than 2 years) birth control method unless other options are considered inadequate. (1, 5.1)

RECENT MAJOR CHANGES

Warnings and Precautions, Meningioma (5.4) | 12/2025

1 INDICATIONS AND USAGE

Medroxyprogesterone Acetate (MPA) Injectable Suspension, USP is a progestin indicated for use by females of reproductive potential to prevent pregnancy. (1)
Limitations of Use:

The use of MPA Injectable Suspension, USP is not recommended as a long-term (i.e., longer than 2 years) birth control method unless other options are considered inadequate. (1, 5.1)

2 DOSAGE AND ADMINISTRATION

The recommended dose is 150 mg of MPA Injectable Suspension, USP every 3 months (13 weeks) administered by deep, intramuscular (IM) injection in the gluteal or deltoid muscle. (2.1)

3 DOSAGE FORMS AND STRENGTHS

- Vials containing sterile aqueous suspension: 150 mg per mL. (3)
- Prefilled syringes: prefilled syringes are available packaged with 22‑gauge × 1 1/2 inch Terumo® SurGuard™ Needles. (3)

4 CONTRAINDICATIONS

- Active thrombophlebitis, or current or past history of thromboembolic disorders, or cerebral vascular disease. (4)
- Known or suspected malignancy of breast. (4)
- Known hypersensitivity to MPA Injectable Suspension, USP (medroxyprogesterone acetate or any of its other ingredients). (4)
- Significant liver disease. (4)
- Undiagnosed vaginal bleeding. (4)

5 WARNINGS AND PRECAUTIONS

- Thromboembolic Disorders: Discontinue MPA Injectable Suspension, USP in patients who develop thrombosis. (5.2)
- Cancer Risks: Monitor women with a strong family history of breast cancer carefully. (5.3)
- Meningioma: Discontinue MPA Injectable Suspension, USP if meningioma is diagnosed. Monitor patients for signs and symptoms of meningioma. (5.4)
- Ectopic Pregnancy: Consider ectopic pregnancy if a woman using MPA Injectable Suspension, USP becomes pregnant or complains of severe abdominal pain. (5.5)
- Anaphylaxis and Anaphylactoid Reactions: Provide emergency medical treatment. (5.6)
- Liver Function: Discontinue MPA Injectable Suspension, USP if jaundice or disturbances of liver function develop. (5.8)
- Carbohydrate Metabolism: Monitor diabetic patients carefully. (5.13)

6 ADVERSE REACTIONS

Most common adverse reactions (incidence >5%): menstrual irregularities (bleeding or spotting) 57% at 12 months, 32% at 24 months, abdominal pain/discomfort 11%, weight gain >10 lb at 24 months 38%, dizziness 6%, headache 17%, nervousness 11%, decreased libido 6%. (6.1)
To report SUSPECTED ADVERSE REACTIONS, contact Prasco Laboratories at 1-866-525-0688 or FDA at 1-800-FDA-1088 or www.fda.gov/medwatch.

7 DRUG INTERACTIONS

Drugs or herbal products that induce certain enzymes, including CYP3A4, may decrease the effectiveness of contraceptive drug products. Counsel patients to use a back-up method or alternative method of contraception when enzyme inducers are used with MPA Injectable Suspension, USP. (7.1)

8 USE IN SPECIFIC POPULATIONS

- Pregnancy: Discontinue if pregnancy occurs. (8.1)
- Lactation: Detectable amounts of drug have been identified in the milk of mothers receiving MPA Injectable Suspension, USP. (8.2)
- Pediatric Patients: MPA Injectable Suspension, USP is not indicated before menarche. (8.4)

FULL PRESCRIBING INFORMATION

WARNING: LOSS OF BONE MINERAL DENSITY

- Women who use Medroxyprogesterone Acetate (MPA) Injectable Suspension, USP may lose significant bone mineral density. Bone loss is greater with increasing duration of use and may not be completely reversible [see Warnings and Precautions (5.1)].
- It is unknown if use of MPA Injectable Suspension, USP during adolescence or early adulthood, a critical period of bone accretion, will reduce peak bone mass and increase the risk for osteoporotic fracture in later life [see Warnings and Precautions (5.1)].
- MPA Injectable Suspension, USP is not recommended as a long-term (i.e., longer than 2 years) birth control method unless other options are considered inadequate [see Indications and Usage (1) and Warnings and Precautions (5.1)].

1 INDICATIONS AND USAGE

Medroxyprogesterone Acetate (MPA) Injectable Suspension, USP is indicated for use by females of reproductive potential to prevent pregnancy.

Limitations of Use:

The use of MPA Injectable Suspension, USP is not recommended as a long‑term (i.e., longer than 2 years) birth control method unless other options are considered inadequate [see Dosage and Administration (2.1) and Warnings and Precautions (5.1)].

2 DOSAGE AND ADMINISTRATION

2.1 Prevention of Pregnancy

Both the 1 mL vial and the 1 mL prefilled syringe of MPA Injectable Suspension, USP should be vigorously shaken just before use to ensure that the dose being administered represents a uniform suspension.

The recommended dose is 150 mg of MPA Injectable Suspension, USP every 3 months (13 weeks) administered by deep intramuscular (IM) injection using strict aseptic technique in the gluteal or deltoid muscle, rotating the sites with every injection. As with any IM injection, to avoid an inadvertent subcutaneous injection, body habitus should be assessed prior to each injection to determine if a longer needle is necessary particularly for gluteal IM injection.

Use for longer than 2 years is not recommended (unless other birth control methods are considered inadequate) due to the impact of long-term MPA Injectable Suspension, USP treatment on bone mineral density (BMD) [see Warnings and Precautions (5.1)]. Dosage does not need to be adjusted for body weight [see Clinical Studies (14.1)].

To ensure the patient is not pregnant at the time of the first injection, the first injection should be given ONLY during the first 5 days of a normal menstrual period or within the first 5-days post‑partum. In post-partum mothers who exclusively breastfeed, administer MPA Injectable Suspension, USP during or after the sixth post‑partum week. If the time interval between injections is greater than 13 weeks, the physician should determine that the patient is not pregnant before administering the drug. The efficacy of MPA Injectable Suspension, USP depends on adherence to the dosage schedule of administration.

2.2 Switching from Other Methods of Contraception

When switching from other contraceptive methods, MPA Injectable Suspension, USP should be given in a manner that ensures continuous contraceptive coverage based upon the mechanism of action of both methods, (e.g., patients switching from oral contraceptives should have their first injection of MPA Injectable Suspension, USP on the day after the last active tablet or at the latest, on the day following the final inactive tablet).

3 DOSAGE FORMS AND STRENGTHS

Sterile Aqueous suspension: 150 mg/mL

Prefilled syringes are available packaged with 22-gauge × 1 1/2 inch Terumo® SurGuard™ Needles.

4 CONTRAINDICATIONS

The use of MPA Injectable Suspension, USP is contraindicated in the following conditions:

- Active thrombophlebitis, or current or history of thromboembolic disorders, or cerebral vascular disease [see Warnings and Precautions (5.2)].
- Known or suspected malignancy of breast [see Warnings and Precautions (5.3)].
- Known hypersensitivity to MPA Injectable Suspension, USP (medroxyprogesterone acetate or any of its other ingredients) [see Warnings and Precautions (5.6)].
- Significant liver disease [see Warnings and Precautions (5.8)].
- Undiagnosed vaginal bleeding [see Warnings and Precautions (5.11)].

5 WARNINGS AND PRECAUTIONS

5.1 Loss of Bone Mineral Density

Use of MPA Injectable Suspension, USP reduces serum estrogen levels and is associated with significant loss of bone mineral density (BMD). This loss of BMD is of particular concern during adolescence and early adulthood, a critical period of bone accretion. It is unknown if use of MPA Injectable Suspension, USP by younger women will reduce peak bone mass and increase the risk for osteoporotic fracture in later life.

A study to assess the reversibility of loss of BMD in adolescents was conducted with MPA Injectable Suspension, USP. After discontinuing MPA Injectable Suspension, USP in these adolescents, mean BMD loss at the total hip and femoral neck did not fully recover by 5 years (60 months) post-treatment in the sub-group of adolescents who were treated for more than 2 years [see Clinical Studies (14.3)]. Similarly, in adults, there was only partial recovery of mean BMD at the total hip, femoral neck, and lumbar spine towards baseline by 2 years post-treatment [see Clinical Studies (14.2)].

The use of MPA Injectable Suspension, USP is not recommended as a long-term (i.e., longer than 2 years) birth control method unless other options are considered inadequate. BMD should be evaluated when a woman needs to continue to use MPA Injectable Suspension, USP long-term. In adolescents, interpretation of BMD results should take into account patient age and skeletal maturity.

Other birth control methods should be considered in the risk/benefit analysis for the use of MPA Injectable Suspension, USP in women with osteoporosis risk factors. MPA Injectable Suspension, USP can pose an additional risk in patients with risk factors for osteoporosis (e.g., metabolic bone disease, chronic alcohol and/or tobacco use, anorexia nervosa, strong family history of osteoporosis or chronic use of drugs that can reduce bone mass such as anticonvulsants or corticosteroids).

5.2 Thromboembolic Disorders

There have been reports of serious thrombotic events in women using MPA Injectable Suspension, USP (150 mg). However, MPA Injectable Suspension, USP has not been causally associated with the induction of thrombotic or thromboembolic disorders. Any patient who develops thrombosis while undergoing therapy with MPA Injectable Suspension, USP should discontinue treatment unless she has no other acceptable options for birth control.

Do not re-administer MPA Injectable Suspension, USP pending examination if there is a sudden partial or complete loss of vision or if there is a sudden onset of proptosis, diplopia, or migraine. Do not re-administer if examination reveals papilledema or retinal vascular lesions.

5.3 Cancer Risks

Breast Cancer

Women who have or have had a history of breast cancer should not use hormonal contraceptives, including MPA Injectable Suspension, USP, because breast cancer may be hormonally sensitive [see Contraindications (4)]. Women with a strong family history of breast cancer should be monitored with particular care.

The results of five large case-control studies assessing the association between depo-medroxyprogesterone acetate (DMPA) use and the risk of breast cancer are summarized in Figure 1. Three of the studies suggest a slightly increased risk of breast cancer in the overall population of users; these increased risks were statistically significant in one study. One recent US study^1 evaluated the recency and duration of use and found a statistically significantly increased risk of breast cancer in recent users (defined as last use within the past five years) who used DMPA for 12 months or longer; this is consistent with results of a previous study^2.

Figure 1. Risk estimates for breast cancer in DMPA users

Odds ratio estimates were adjusted for the following covariates:
Lee et al. (1987): age, parity, and socioeconomic status.
Paul et al. (1989): age, parity, ethnic group, and year of interview.
WHO (1991): age, center, and age at first live birth.
Shapiro et al. (2000): age, ethnic group, socioeconomic status, and any combined estrogen/progestogen oral contraceptive use.
Li et al. (2012): age, year, BMI, duration of OC use, number of full-term pregnancies, family history of breast cancer, and history of screening mammography.

Based on the published SEER-18 2011 incidence rate (age-adjusted to the 2000 US Standard Population) of breast cancer for US women, all races, age 20 to 49 years, a doubling of risk would increase the incidence of breast cancer in women who use MPA Injectable Suspension, USP from about 72 to about 144 cases per 100,000 women.

Cervical Cancer

A statistically nonsignificant increase in relative risk (RR) estimates of invasive squamous-cell cervical cancer has been associated with the use of MPA Injectable Suspension, USP in women who were first exposed before the age of 35 years (RR 1.22 to 1.28 and 95% CI 0.93 to 1.70). The overall, nonsignificant RR of invasive squamous-cell cervical cancer in women who ever used MPA Injectable Suspension, USP was estimated to be 1.11 (95% CI 0.96 to 1.29). No trends in risk with duration of use or times since initial or most recent exposure were observed.

Other Cancers

Long-term case-controlled surveillance of users of MPA Injectable Suspension, USP found no overall increased risk of ovarian or liver cancer.

5.4 Meningioma

Cases of meningiomas have been reported following repeated administration of medroxyprogesterone acetate, primarily with long term use. Monitor patients on MPA Injectable Suspension, USP for signs and symptoms of meningioma. Discontinue MPA Injectable Suspension, USP if a meningioma is diagnosed.

5.5 Ectopic Pregnancy

Be alert to the possibility of an ectopic pregnancy among women using MPA Injectable Suspension, USP who become pregnant or complain of severe abdominal pain.

5.6 Anaphylaxis and Anaphylactoid Reaction

Anaphylaxis and anaphylactoid reaction have been reported with the use of MPA Injectable Suspension, USP. Institute emergency medical treatment if an anaphylactic reaction occurs.

5.7 Injection Site Reactions

Injection site reactions have been reported with use of MPA Injectable Suspension, USP [see Adverse Reactions (6.2)]. Persistent injection site reactions may occur after administration of MPA Injectable Suspension, USP due to inadvertent subcutaneous administration or release of the drug into the subcutaneous space while removing the needle [see Dosage and Administration (2.1)].

5.8 Liver Function

Discontinue MPA Injectable Suspension, USP use if jaundice or acute or chronic disturbances of liver function develop. Do not resume use until markers of liver function return to normal and MPA Injectable Suspension, USP causation has been excluded.

5.9 Convulsions

There have been a few reported cases of convulsions in patients who were treated with MPA Injectable Suspension, USP. Association with drug use or pre-existing conditions is not clear.

5.10 Depression

Monitor patients who have a history of depression and do not re-administer MPA Injectable Suspension, USP if depression recurs.

5.11 Bleeding Irregularities

Most women using MPA Injectable Suspension, USP experience disruption of menstrual bleeding patterns. Altered menstrual bleeding patterns include amenorrhea, irregular or unpredictable bleeding or spotting, prolonged spotting or bleeding, and heavy bleeding. Rule out the possibility of organic pathology if abnormal bleeding persists or is severe, and institute appropriate treatment.

As women continue using MPA Injectable Suspension, USP, fewer experience irregular bleeding and more experience amenorrhea. In clinical studies of MPA Injectable Suspension, USP, by month 12 amenorrhea was reported by 55% of women, and by month 24, amenorrhea was reported by 68% of women using MPA Injectable Suspension, USP.

5.12 Weight Gain

Women tend to gain weight while on therapy with MPA Injectable Suspension, USP. From an initial average body weight of 136 lb, women who completed 1 year of therapy with MPA Injectable Suspension, USP gained an average of 5.4 lb. Women who completed 2 years of therapy gained an average of 8.1 lb. Women who completed 4 years gained an average of 13.8 lb. Women who completed 6 years gained an average of 16.5 lb. Two percent of women withdrew from a large-scale clinical trial because of excessive weight gain.

5.13 Carbohydrate Metabolism

A decrease in glucose tolerance has been observed in some patients on MPA Injectable Suspension, USP treatment. Monitor diabetic patients carefully while receiving MPA Injectable Suspension, USP.

5.14 Fluid Retention

Because progestational drugs including MPA Injectable Suspension, USP may cause some degree of fluid retention, monitor patients with conditions that might be influenced by this condition, such as epilepsy, migraine, asthma, and cardiac or renal dysfunction.

5.15 Return of Fertility

Return to ovulation and fertility is likely to be delayed after stopping MPA Injectable Suspension, USP. In a large US study of women who discontinued use of MPA Injectable Suspension, USP to become pregnant, data are available for 61% of them. Of the 188 women who discontinued the study to become pregnant, 114 became pregnant. Based on Life-Table analysis of these data, it is expected that 68% of women who do become pregnant may conceive within 12 months, 83% may conceive within 15 months, and 93% may conceive within 18 months from the last injection. The median time to conception for those who do conceive is 10 months following the last injection with a range of 4 to 31 months, and is unrelated to the duration of use. No data are available for 39% of the patients who discontinued MPA Injectable Suspension, USP to become pregnant and who were lost to follow-up or changed their mind.

5.16 Sexually Transmitted Infections

Patients should be counseled that MPA Injectable Suspension, USP does not protect against HIV infection (AIDS) and other sexually transmitted infections.

5.17 Monitoring

A woman who is taking hormonal contraceptive should have a yearly visit with her healthcare professional for a blood pressure check and for other indicated healthcare.

5.18 Interference with Laboratory Tests

The use of MPA Injectable Suspension, USP may change the results of some laboratory tests, such as coagulation factors, lipids, glucose tolerance, and binding proteins [see Drug Interactions (7.2)].

6 ADVERSE REACTIONS

The following important adverse reactions observed with the use of MPA Injectable Suspension, USP are discussed in greater detail in the Warnings and Precautions section (5):

- Loss of Bone Mineral Density [see Warnings and Precautions (5.1)]
- Thromboembolic disease [see Warnings and Precautions (5.2)]
- Breast Cancer [see Warnings and Precautions (5.3)]
- Anaphylaxis and Anaphylactoid Reactions [see Warnings and Precautions (5.6)]
- Bleeding Irregularities [see Warnings and Precautions (5.11)]
- Weight Gain [see Warnings and Precautions (5.12)]

6.1 Clinical Trials Experience

Clinical trials are conducted under widely varying conditions, therefore, adverse reaction rates observed in the clinical studies of a drug cannot be directly compared to rates in the clinical trials of another drug and may not reflect the rates observed in practice.

In the two clinical trials with MPA Injectable Suspension, USP, over 3,900 women, who were treated for up to 7 years, reported the following adverse reactions, which may or may not be related to the use of MPA Injectable Suspension, USP. The population studied ranges in age from 15 to 51 years, of which 46% were White, 50% Non-White, and 4.9% Unknown race. The patients received 150 mg MPA Injectable Suspension, USP every 3-months (90 days). The median study duration was 13 months with a range of 1‑84 months. Fifty‑eight percent of patients remained in the study after 13 months and 34% after 24 months.

Table 1. Adverse Reactions that Were Reported by More than 5% of Subjects
Body System [Body System represented from COSTART medical dictionary.] | Adverse Reactions [Incidence (%)]
Body as a Whole | Headache (16.5%) Abdominal pain/discomfort (11.2%)
Metabolic/Nutritional | Increased weight >10 lb at 24 months (37.7%)
Nervous | Nervousness (10.8%) Dizziness (5.6%) Libido decreased (5.5%)
Reproductive (Urogenital^1) | Menstrual irregularities: bleeding (57.3% at 12 months, 32.1% at 24 months) amenorrhea (55% at 12 months, 68% at 24 months)

Table 2. Adverse Reactions that Were Reported by between 1 and 5% of Subjects
Body System [Body System represented from COSTART medical dictionary.] | Adverse Reactions [Incidence (%)]
Body as a Whole | Asthenia/fatigue (4.2%) Backache (2.2%) Dysmenorrhea (1.7%) Hot flashes (1.0%)
Digestive | Nausea (3.3%) Bloating (2.3%)
Metabolic/Nutritional | Edema (2.2%)
Musculoskeletal | Leg cramps (3.7%) Arthralgia (1.0%)
Nervous | Depression (1.5%) Insomnia (1.0%)
Skin and Appendages | Acne (1.2%) No hair growth/alopecia (1.1%) Rash (1.1%)
Reproductive (Urogenital^1) | Leukorrhea (2.9%) Breast pain (2.8%) Vaginitis (1.2%)

Adverse reactions leading to study discontinuation in ≥2% of subjects: bleeding (8.2%), amenorrhea (2.1%), weight gain (2.0%).

6.2 Post-Marketing Experience

The following adverse reactions have been identified during post approval use of MPA Injectable Suspension, USP. Because these reactions are reported voluntarily from a population of uncertain size, it is not always possible to reliably estimate their frequency or establish a causal relationship to drug exposure.

There have been cases of osteoporosis including osteoporotic fractures reported post-marketing in patients taking MPA Injectable Suspension, USP.

Table 3. Adverse Reactions Reported during Post-Marketing Experience
Body System [Body System represented from COSTART medical dictionary.] | Adverse Reactions
Body as a Whole | Chest pain, Allergic reactions including angioedema, Fever, Injection site abscess [Injection site abscess and injection site infections have been reported; therefore, strict aseptic injection technique should be followed when administering MPA Injectable Suspension, USP in order to avoid injection site infections [see Dosage and Administration (2.1)].] , Injection site infection, Injection site nodule/lump, Injection site pain/tenderness, Injection site persistent atrophy/indentation/dimpling, Injection-site reaction, Lipodystrophy acquired, Chills, Axillary swelling
Cardiovascular | Syncope, Tachycardia, Thrombophlebitis, Deep vein thrombosis, Pulmonary embolus, Varicose veins
Digestive | Changes in appetite, Gastrointestinal disturbances, Jaundice, Excessive thirst, Rectal bleeding
Hematologic and Lymphatic | Anemia, Blood dyscrasia
Musculoskeletal | Osteoporosis
Neoplasms | Cervical cancer, Breast cancer
Nervous | Paralysis, Facial palsy, Paresthesia, Drowsiness
Respiratory | Dyspnea and asthma, Hoarseness
Skin and Appendages | Hirsutism, Excessive sweating and body odor, Dry skin, Scleroderma, Melasma, Chloasma
Reproductive (Urogenital^1) | Lack of return to fertility, Unexpected pregnancy, Changes in breast size, Breast lumps or nipple bleeding, Galactorrhea, Increased libido, Uterine hyperplasia, Vaginal cysts, Genitourinary infections, Dyspareunia

7 DRUG INTERACTIONS

7.1 Changes in Contraceptive Effectiveness Associated with Co-Administration of Other Products

If a woman on hormonal contraceptives takes a drug or herbal product that induces enzymes, including CYP3A4, that metabolize contraceptive hormones, counsel her to use additional contraception or a different method of contraception. Drugs or herbal products that induce such enzymes may decrease the plasma concentrations of contraceptive hormones, and may decrease the effectiveness of hormonal contraceptives. Some drugs or herbal products that may decrease the effectiveness of hormonal contraceptives include:

- barbiturates
- bosentan
- carbamazepine
- felbamate
- griseofulvin
- oxcarbazepine
- phenytoin
- rifampin
- St. John's wort
- topiramate

HIV protease inhibitors and non-nucleoside reverse transcriptase inhibitors: Significant changes (increase or decrease) in the plasma levels of progestin have been noted in some cases of co-administration of HIV protease inhibitors. Significant changes (increase or decrease) in the plasma levels of the progestin have been noted in some cases of co-administration with non-nucleoside reverse transcriptase inhibitors.

Antibiotics: There have been reports of pregnancy while taking hormonal contraceptives and antibiotics, but clinical pharmacokinetic studies have not shown consistent effects of antibiotics on plasma concentrations of synthetic steroids.

Consult the labeling of all concurrently-used drugs to obtain further information about interactions with hormonal contraceptives or the potential for enzyme alterations.

7.2 Laboratory Test Interactions

The pathologist should be advised of progestin therapy when relevant specimens are submitted.

The following laboratory tests may be affected by progestins including MPA Injectable Suspension, USP:

(a) Plasma and urinary steroid levels are decreased (e.g., progesterone, estradiol, pregnanediol, testosterone, cortisol).
(b) Gonadotropin levels are decreased.
(c) Sex-hormone-binding-globulin concentrations are decreased.
(d) Protein-bound iodine and butanol extractable protein-bound iodine may increase. T3-uptake values may decrease.
(e) Coagulation test values for prothrombin (Factor II), and Factors VII, VIII, IX, and X may increase.
(f) Sulfobromophthalein and other liver function test values may be increased.
(g) The effects of medroxyprogesterone acetate on lipid metabolism are inconsistent. Both increases and decreases in total cholesterol, triglycerides, low-density lipoprotein (LDL) cholesterol, and high-density lipoprotein (HDL) cholesterol have been observed in studies.

8 USE IN SPECIFIC POPULATIONS

8.1 Pregnancy

Risk Summary

There is no use for contraception in pregnancy; therefore, MPA Injectable Suspension, USP should be discontinued during pregnancy.

Epidemiologic studies and meta-analyses have not found an increased risk of genital or non-genital birth defects (including cardiac anomalies and limb-reduction defects) following exposure to progestins before conception or during early pregnancy.

All pregnancies have a background risk of birth defect, loss, or other adverse outcomes. In the U.S. general population, the estimated background risk of major birth defects and miscarriage in clinically recognized pregnancies is 2-4% and 15-20%, respectively.

8.2 Lactation

Risk Summary

Although medroxyprogesterone acetate is detectable in the milk of mothers receiving MPA Injectable Suspension, USP, milk composition, quality, and amount do not appear to be adversely affected. Effects on milk production and lactation initiation/duration remain unclear when administered before 6 weeks after delivery, therefore, in mothers who exclusively breastfeed, initiate MPA Injectable Suspension, USP during or after the sixth post-partum week [see Dosage and Administration (2.1)].

No adverse effects in breastfed infants would be expected with maternal use of progestins. Neonates and infants exposed to medroxyprogesterone acetate from breast milk have been studied and no adverse effects have been noted.

The developmental and health benefits of breast-feeding should be considered along with the mother’s clinical need for MPA Injectable Suspension, USP and any potential adverse effects on the breastfed child from MPA Injectable Suspension, USP or from the underlying maternal condition.

8.3 Females and Males of Reproductive Potential

MPA Injectable Suspension, USP is indicated for the prevention of pregnancy and would therefore be expected to impair female fertility until cessation of treatment. Women may experience a delay in return to ovulation and fertility (conception) following discontinuation of MPA Injectable Suspension, USP [see Warnings and Precautions (5.15)].

8.4 Pediatric Use

MPA Injectable Suspension, USP is not indicated before menarche. Use of MPA Injectable Suspension, USP is associated with significant loss of BMD. This loss of BMD is of particular concern during adolescence and early adulthood, a critical period of bone accretion. In adolescents, interpretation of BMD results should take into account patient age and skeletal maturity. It is unknown if use of MPA Injectable Suspension, USP by younger women will reduce peak bone mass and increase the risk of osteoporotic fractures in later life. Other than concerns about loss of BMD, the safety and effectiveness are expected to be the same for postmenarchal adolescents and adult women.

8.5 Geriatric Use

This product has not been studied in post-menopausal women and is not indicated in this population.

11 DESCRIPTION

Medroxyprogesterone Acetate Injectable Suspension, USP contains medroxyprogesterone acetate, a derivative of progesterone, as its active ingredient. Medroxyprogesterone acetate is active by the parenteral and oral routes of administration. It is a white to off-white; odorless crystalline powder that is stable in air and that melts between 200°C and 210°C. It is freely soluble in chloroform, soluble in acetone and dioxane, sparingly soluble in alcohol and methanol, slightly soluble in ether, and insoluble in water.

The chemical name for medroxyprogesterone acetate is pregn-4-ene-3, 20-dione, 17-(acetyloxy)-6-methyl-, (6α-).

The structural formula is as follows:

MPA Injectable Suspension, USP for IM injection is available in vials and prefilled syringes, each containing 1 mL of medroxyprogesterone acetate sterile aqueous suspension 150 mg/mL.

For MPA Injectable Suspension, USP vials, each mL of sterile aqueous suspension contains:

Medroxyprogesterone acetate | 150 mg
Polyethylene glycol 3350 | 28.9 mg
Polysorbate 80 | 2.41 mg
Sodium chloride | 8.68 mg
Methylparaben | 1.37 mg
Propylparaben | 0.150 mg
Water for injection | quantity sufficient

When necessary, pH is adjusted with sodium hydroxide or hydrochloric acid, or both.

For MPA Injectable Suspension, USP prefilled syringes, each mL of sterile aqueous suspension contains:

Medroxyprogesterone acetate | 150 mg
Polyethylene glycol 3350 | 28.5 mg
Polysorbate 80 | 2.37 mg
Sodium chloride | 8.56 mg
Methylparaben | 1.35 mg
Propylparaben | 0.147 mg
Water for injection | quantity sufficient

When necessary, pH is adjusted with sodium hydroxide or hydrochloric acid, or both.

12 CLINICAL PHARMACOLOGY

12.1 Mechanism of Action

MPA Injectable Suspension, USP inhibits the secretion of gonadotropins which primarily prevents follicular maturation and ovulation and causes thickening of cervical mucus. These actions contribute to its contraceptive effect.

12.2 Pharmacodynamics

No specific pharmacodynamic studies were conducted with MPA Injectable Suspension, USP.

12.3 Pharmacokinetics

Absorption

Following a single 150 mg IM dose of MPA Injectable Suspension, USP in eight women between the ages of 28 and 36 years old, medroxyprogesterone acetate concentrations, measured by an extracted radioimmunoassay procedure, increase for approximately 3 weeks to reach peak plasma concentrations of 1 to 7 ng/mL.

Distribution

Plasma protein binding of medroxyprogesterone acetate averages 86%. Medroxyprogesterone acetate binding occurs primarily to serum albumin. No binding of medroxyprogesterone acetate occurs with sex-hormone-binding globulin (SHBG).

Elimination

Metabolism

Medroxyprogesterone acetate is extensively metabolized in the liver by P450 enzymes. Its metabolism primarily involves ring A and/or side-chain reduction, loss of the acetyl group, hydroxylation in the 2-, 6-, and 21-positions or a combination of these positions, resulting in more than 10 metabolites.

Excretion

The concentrations of medroxyprogesterone acetate decrease exponentially until they become undetectable (<100 pg/mL) between 120 to 200 days following injection. Using an unextracted radioimmunoassay procedure for the assay of medroxyprogesterone acetate in serum, the apparent half-life for medroxyprogesterone acetate following IM administration of MPA Injectable Suspension, USP is approximately 50 days. Most medroxyprogesterone acetate metabolites are excreted in the urine as glucuronide conjugates with only minor amounts excreted as sulfates.

Specific Populations

The effect of hepatic and/or renal impairment on the pharmacokinetics of MPA Injectable Suspension, USP is unknown.

13 NONCLINICAL TOXICOLOGY

13.1 Carcinogenesis, Mutagenesis, Impairment of Fertility

[see Warnings and Precautions (5.3, 5.15) and Use in Specific Populations (8.3)].

14 CLINICAL STUDIES

14.1 Contraception

In five clinical studies using MPA Injectable Suspension, USP, the 12-month failure rate for the group of women treated with MPA Injectable Suspension, USP was zero (no pregnancies reported) to 0.7 by Life-Table method. The effectiveness of MPA Injectable Suspension, USP is dependent on the patient returning every 3 months (13 weeks) for reinjection.

14.2 Bone Mineral Density Changes in Women Treated with MPA Injectable Suspension, USP

In a controlled, clinical study, adult women using MPA Injectable Suspension, USP (150 mg) for up to 5 years showed spine and hip bone mineral density (BMD) mean decreases of 5–6%, compared to no significant change in BMD in the control group. The decline in BMD was more pronounced during the first two years of use, with smaller declines in subsequent years. Mean changes in lumbar spine BMD of -2.86%, ‑4.11%, ‑4.89%, ‑4.93% and ‑5.38% after 1, 2, 3, 4, and 5 years, respectively, were observed. Mean decreases in BMD of the total hip and femoral neck were similar.

After stopping use of MPA Injectable Suspension, USP, there was partial recovery of BMD toward baseline values during the 2-year post-therapy period. Longer duration of treatment was associated with less complete recovery during this 2-year period following the last injection. Table 4 shows the change in BMD in women after 5 years of treatment with MPA Injectable Suspension, USP and in women in a control group, as well as the extent of recovery of BMD for the subset of the women for whom 2-year post treatment data were available.

Table 4. Mean Percent Change from Baseline in BMD in Adults by Skeletal Site and Cohort (5 Years of Treatment and 2 Years of Follow-Up)
Time in Study | Spine |  | Total Hip |  | Femoral Neck
 | Medroxy-progesterone Acetate [The treatment group consisted of women who received MPA Injectable Suspension, USP for 5 years and were then followed for 2 years post-use (total time in study of 7 years).] | Control [The control group consisted of women who did not use hormonal contraception and were followed for 7 years.] | Medroxy-progesterone Acetate | Control | Medroxy-progesterone Acetate | Control
5 years | -5.38% n=33 | 0.43% n=105 | -5.16% n=21 | 0.19% n=65 | -6.12% n=34 | -0.27% n=106
7 years | -3.13% n=12 | 0.53% n=60 | -1.34% n=7 | 0.94% n=39 | -5.38% n=13 | -0.11% n=63

14.3 Bone Mineral Density Changes in Adolescent Females (12 to 18 Years of Age) Treated with MPA Injectable Suspension, USP

The impact of MPA Injectable Suspension, USP (150 mg) use for up to 240 weeks (4.6 years) was evaluated in an open-label non-randomized clinical study in 389 adolescent females (12 to 18 years of age). Use of MPA Injectable Suspension, USP was associated with a significant decline from baseline in BMD.

Partway through the trial, drug administration was stopped (at 120 weeks). The mean number of injections per MPA Injectable Suspension, USP user was 9.3. Table 5 summarizes the study findings. The decline in BMD at total hip and femoral neck was greater with longer duration of use. The mean decrease in BMD at 240 weeks was more pronounced at total hip (-6.4%) and femoral neck (-5.4%) compared to lumbar spine (-2.1%).

Adolescents in the untreated cohort had an increase in BMD during the period of growth following menarche. However, the two cohorts were not matched at baseline for age, gynecologic age, race, BMD and other factors that influence the rate of acquisition of BMD.

Table 5. BMD Mean Percent Change from Baseline in Adolescents Receiving ≥4 Injections per 60-week Period, by Skeletal Site and Cohort
Duration of Treatment | MPA Injectable Suspension, USP (150 mg IM) |  | Unmatched, Untreated Cohort
 | N | Mean % Change | N | Mean % Change
Total Hip BMD
Week 60 (1.2 years) | 113 | -2.75 | 166 | 1.22
Week 120 (2.3 years) | 73 | -5.40 | 109 | 2.19
Week 240 (4.6 years) | 28 | -6.40 | 84 | 1.71
Femoral Neck BMD
Week 60 | 113 | -2.96 | 166 | 1.75
Week 120 | 73 | -5.30 | 108 | 2.83
Week 240 | 28 | -5.40 | 84 | 1.94
Lumbar Spine BMD
Week 60 | 114 | -2.47 | 167 | 3.39
Week 120 | 73 | -2.74 | 109 | 5.28
Week 240 | 27 | -2.11 | 84 | 6.40

BMD Recovery Post-Treatment in Adolescents

Longer duration of treatment and smoking were associated with less recovery of BMD following the last injection of MPA Injectable Suspension, USP. Table 6 shows the extent of recovery of BMD up to 60 months post-treatment for adolescents who received MPA Injectable Suspension, USP for two years or less compared to more than two years. Post-treatment follow-up showed that, in women treated for more than two years, only lumbar spine BMD recovered to baseline levels after treatment was discontinued. Adolescents treated with MPA Injectable Suspension, USP for more than two years did not recover to their baseline BMD level at femoral neck and total hip even up to 60 months post-treatment. Adolescents in the untreated cohort gained BMD throughout the trial period (data not shown) [see Warnings and Precautions (5.1)].

Table 6. BMD Recovery (Months Post-Treatment) in Adolescents by Years of MPA Injectable Suspension, USP Use (2 Years or Less vs. More than 2 Years)
Duration of Treatment | 2 years or less |  | More than 2 years
 | N | Mean % Change from baseline | N | Mean % Change from baseline
Total Hip BMD
End of Treatment | 49 | -1.5% | 49 | -6.2%
12 M post-treatment | 33 | -1.4% | 24 | -4.6%
24 M post-treatment | 18 | 0.3% | 17 | -3.6%
36 M post-treatment | 12 | 2.1% | 11 | -4.6%
48 M post-treatment | 10 | 1.3% | 9 | -2.5%
60 M post-treatment | 3 | 0.2% | 2 | -1.0%
Femoral Neck BMD
End of Treatment | 49 | -1.6% | 49 | -5.8%
12 M post-treatment | 33 | -1.4% | 24 | -4.3%
24 M post-treatment | 18 | 0.5% | 17 | -3.8%
36 M post-treatment | 12 | 1.2% | 11 | -3.8%
48 M post-treatment | 10 | 2.0% | 9 | -1.7%
60 M post-treatment | 3 | 1.0% | 2 | -1.9%
Lumbar Spine BMD
End of Treatment | 49 | -0.9% | 49 | -3.5%
12 M post-treatment | 33 | 0.4% | 23 | -1.1%
24 M post-treatment | 18 | 2.6% | 17 | 1.9%
36 M post-treatment | 12 | 2.4% | 11 | 0.6%
48 M post-treatment | 10 | 6.5% | 9 | 3.5%
60 M post-treatment | 3 | 6.2% | 2 | 5.7%

14.4 Bone Fracture Incidence in Women Treated with MPA Injectable Suspension, USP

A retrospective cohort study to assess the association between MPA Injectable Suspension, USP and the incidence of bone fractures was conducted in 312,395 female contraceptive users in the UK. The incidence rates of fracture were compared between MPA Injectable Suspension, USP users and contraceptive users who had no recorded use of MPA Injectable Suspension, USP. The Incident Rate Ratio (IRR) for any fracture during the follow-up period (mean=5.5 years) was 1.41 (95% CI 1.35, 1.47). It is not known if this is due to MPA Injectable Suspension, USP use or to other related lifestyle factors that have a bearing on fracture rate.

In the study, when cumulative exposure to MPA Injectable Suspension, USP was calculated, the fracture rate in users who received fewer than 8 injections was higher than that in women who received 8 or more injections. However, it is not clear that cumulative exposure, which may include periods of intermittent use separated by periods of non-use, is a useful measure of risk, as compared to exposure measures based on continuous use.

There were very few osteoporotic fractures (fracture sites known to be related to low BMD) in the study overall, and the incidence of osteoporotic fractures was not found to be higher in MPA Injectable Suspension, USP users compared to non-users.

Importantly, this study could not determine whether use of MPA Injectable Suspension, USP has an effect on fracture rate later in life.

15 REFERENCES

1. Li CI, Beaber EF, Tang, MCT et al. Effect of Depo-Medroxyprogesterone Acetate on Breast Cancer Risk among Women 20 to 44 years of Age. Cancer Research 2012; 72:2028–2035.
2. Paul C, Skegg DCG, Spears GFS. Depot medroxyprogesterone (Depo-Provera) and risk of breast cancer. Br Med J 1989; 299:759–62.

16 HOW SUPPLIED/STORAGE AND HANDLING

Product: 50090-5619

NDC: 50090-5619-0 1 mL in a VIAL / 1 in a CARTON

17 PATIENT COUNSELING INFORMATION

Advise the patient to read the FDA‑approved patient labeling (Patient Information).

- Advise patients at the beginning of treatment that their menstrual cycle may be disrupted and that irregular and unpredictable bleeding or spotting results, and that this usually decreases to the point of amenorrhea as treatment with MPA Injectable Suspension, USP continues, without other therapy being required.
- Counsel patients about the possible increased risk of breast cancer in women who use MPA Injectable Suspension, USP [see Warnings and Precautions (5.3)].
- Counsel patients with a history of meningioma about the possible risk of worsening meningioma [see Warnings and Precautions (5.4)].
- Counsel patients that this product does not protect against HIV infection (AIDS) and other sexually transmitted infections.
- Counsel patients on Warnings and Precautions associated with use of MPA Injectable Suspension, USP.
- Counsel patients to use a back-up method or alternative method of contraception when enzyme inducers are used with MPA Injectable Suspension, USP.

Distributed by:
Prasco Laboratories
Mason, OH 45040 USA

LAB-1462-5.0

Patient Information

Medroxyprogesterone Acetate Injectable Suspension, USP
Contraceptive Injection

Read this Patient Information carefully before you decide if Medroxyprogesterone Acetate (MPA) Injectable Suspension, USP is right for you. This information does not take the place of talking with your gynecologist or other healthcare professional who specializes in women's health. If you have any questions about MPA Injectable Suspension, USP, ask your healthcare professional. You should also learn about other birth control methods to choose the one that is best for you.

What is the most important information I should know about MPA Injectable Suspension, USP?

MPA Injectable Suspension, USP can cause serious side effects, including:

- Use of MPA Injectable Suspension, USP may cause you to lose calcium stored in your bone and decrease your bone mass. The longer you use MPA Injectable Suspension, USP, the greater your loss of calcium from your bones. Your bones may not recover completely when you stop using MPA Injectable Suspension, USP.
- If you use MPA Injectable Suspension, USP continuously for a long time (for more than 2 years), it may increase the risk of weak, porous bones (osteoporosis) that could increase the risk of broken bones, especially after menopause.
- You should not use MPA Injectable Suspension, USP for more than two years unless you cannot use other birth control methods.
- It is not known if your risk of developing osteoporosis is greater if you are a teenager or young adult when you start to use MPA Injectable Suspension, USP. (see "What are the possible side effects of MPA Injectable Suspension, USP?").

MPA Injectable Suspension, USP is intended to prevent pregnancy. MPA Injectable Suspension, USP does not protect against HIV infection (AIDS) and other sexually transmitted infections (STIs).

What is MPA Injectable Suspension, USP?

MPA Injectable Suspension, USP is a progestin hormone birth control method that is given by injection (a shot) to prevent pregnancy.

How well does MPA Injectable Suspension, USP work?

Your chance of getting pregnant depends on how well you follow the directions for taking your MPA Injectable Suspension, USP. The more carefully you follow the directions (such as returning every 3 months for your next injection), the less chance you have of getting pregnant.

In clinical studies, about 1 out of 100 women got pregnant during the first year that they used MPA Injectable Suspension, USP.

The following chart shows the chance of getting pregnant for women who use different methods of birth control. Each box on the chart contains a list of birth control methods that are similar in effectiveness. The most effective methods are at the top of the chart. The box on the bottom of the chart shows the chance of getting pregnant for women who do not use birth control and are trying to get pregnant.

How should I take MPA Injectable Suspension, USP?

- MPA Injectable Suspension, USP is given by your healthcare professional as a shot into your muscle (intramuscular injection). The shot is given in your buttock or upper arm 1 time every 3 months. At the end of the 3 months, you will need to return to your healthcare professional for your next injection in order to continue your protection against pregnancy.
- To make sure that you are not pregnant before you take MPA Injectable Suspension, USP, the first injection should be given only:
  - during the first 5 days of a normal menstrual period, or
  - within the first 5 days after giving birth, if you are not breastfeeding, or
  - at the 6th week after giving birth, if you are feeding your baby only breastmilk.
- MPA Injectable Suspension, USP may be given at other times than those listed above, but you will likely need to have a pregnancy test first to show that you are not pregnant.
- During treatment with MPA Injectable Suspension, USP, you should see your healthcare professional every year for a blood pressure check and other healthcare needs.

Who Should Not Use MPA Injectable Suspension, USP?

Do not use MPA Injectable Suspension, USP if you:

- have bleeding from your vagina that has not been explained
- have breast cancer now or in the past, or think you have breast cancer
- have had a stroke
- ever had blood clots in your arms, legs or lungs
- have problems with your liver or liver disease
- are allergic to medroxyprogesterone acetate or any of the other ingredients in MPA Injectable Suspension, USP. See the end of this leaflet for a complete list of ingredients in MPA Injectable Suspension, USP.

What should I tell my healthcare professional before taking MPA Injectable Suspension, USP?

Before taking MPA Injectable Suspension, USP, tell your healthcare professional if you have:

- risk factors for weak bones (osteoporosis) such as bone disease, use alcohol or smoke regularly, anorexia nervosa, or a strong family history of osteoporosis
- irregular or lighter than usual menstrual periods
- breast cancer now or in the past, or think you have breast cancer
- a family history of breast cancer
- an abnormal mammogram (breast X-ray), lumps in your breasts, or bleeding from your nipples
- have or have ever had a type of usually benign brain tumor called a meningioma
- kidney problems
- high blood pressure
- had a stroke
- had blood clots in your arms, legs or lungs
- migraine headaches
- asthma
- epilepsy (convulsions or seizures)
- diabetes
- depression or a history of depression
- any other medical conditions

If you are breastfeeding or plan to breastfeed, MPA Injectable Suspension, USP can pass into your breast milk. Talk to your healthcare professional about the best way to feed your baby if you take MPA Injectable Suspension, USP.

Tell your healthcare professional about all of the medicines you take, including prescription and nonprescription medicines, vitamins, and herbal supplements.

MPA Injectable Suspension, USP and certain other medicines may affect each other, causing serious side effects. Sometimes the doses of other medicines may need to be changed while you are taking MPA Injectable Suspension, USP.

Some medicines may make MPA Injectable Suspension, USP less effective at preventing pregnancy, including those listed below.

Especially tell your healthcare professional if you take:

- medicine to help you sleep
- bosentan
- medicine for seizures
- griseofulvin
- an antibiotic
- medicine for HIV (AIDS)
- St. John's wort

Know the medicines you take. Keep a list of your medicines with you to show your healthcare professional or pharmacist before you first start taking MPA Injectable Suspension, USP or when you get a new medicine.

Follow your healthcare professional's instructions about using a back-up method of birth control if you are taking medicines that may make MPA Injectable Suspension, USP less effective.

What are the possible side effects of MPA Injectable Suspension, USP?

MPA Injectable Suspension, USP can cause serious side effects, including:

- Effect on the bones: See “What is the most important information I should know about MPA Injectable Suspension, USP?”.
Teenage years are the most important years to gain bone strength. The decrease in calcium in your bones is of most concern if you are a teenager or have the following problems:
  1. bone disease
  2. an eating disorder (anorexia nervosa)
  3. a strong family history of osteoporosis
  4. you take a drug that can lower the amount of calcium in your bones (drugs for epilepsy or steroid drugs)
  5. you drink a lot of alcohol (more than 2 drinks a day)
  6. you smoke
If you need a birth control method for more than 2 years, your healthcare professional may switch you to another birth control method instead of using MPA Injectable Suspension, USP. If you continue using MPA Injectable Suspension, USP, your healthcare professional may ask you to have a bone test, especially if you have other risks for weak bones.
When MPA Injectable Suspension, USP is stopped, your bones may start to regain calcium. However, in a study of teenage girls who used MPA Injectable Suspension, USP for more than 2 years, their hip bones did not completely recover by 5 years after they stopped using MPA Injectable Suspension, USP. Taking calcium and Vitamin D and exercising daily may lessen the loss of calcium from your bones.
- possible increased risk of breast cancer. Women who use MPA Injectable Suspension, USP may have a slightly increased risk of breast cancer compared to non-users.
- blood clots in your arms, legs, lungs, and eyes
- stroke
- a pregnancy outside of your uterus (ectopic pregnancy). Ectopic pregnancy is a medical emergency that often requires surgery. Ectopic pregnancy can cause internal bleeding, infertility, and even death.
- allergic reactions. Severe allergic reactions have been reported in some women using MPA Injectable Suspension, USP.
- loss of vision or other eye problems
- migraine headaches
- possible increased risk for growth of a meningioma (a usually benign brain tumor), primarily when the product is used for a long time.
- depression
- convulsions or seizures
- liver problems

Call your healthcare professional right away if you have:

- sharp chest pain, coughing up blood, or sudden shortness of breath (indicating a possible clot in the lung)
- sudden severe headache or vomiting, dizziness or fainting, problems with your eyesight or speech, weakness, or numbness in an arm or leg (indicating a possible stroke)
- severe pain or swelling in the calf (indicating a possible clot in the leg)
- sudden blindness, partial or complete (indicating a possible clot in the blood vessels of the eye)
- unusually heavy vaginal bleeding
- severe pain or tenderness in the lower abdominal area
- persistent pain, pus, or bleeding at the injection site
- yellowing of the eyes or skin
- hives
- difficulty breathing
- swelling of the face, mouth, tongue or neck

The most common side effects of MPA Injectable Suspension, USP include:

- irregular vaginal bleeding, such as lighter or heavier menstrual bleeding, or continued spotting
- weight gain. You may experience weight gain while you are using MPA Injectable Suspension, USP. About two-thirds of the women who used MPA Injectable Suspension, USP in the clinical trials reported a weight gain of about 5 pounds during the first year of use. You may continue to gain weight after the first year. Women who used MPA Injectable Suspension, USP for 2 years gained an average of 8 pounds over those 2 years.
- abdominal pain
- headache
- weakness
- tiredness
- nervousness
- dizziness

Tell your healthcare professional if you have any side effect that bothers you or does not go away.

These are not all the possible side effects of MPA Injectable Suspension, USP. For more information, ask your healthcare professional or pharmacist.

Call your doctor for medical advice about side effects. You may report side effects to FDA at 1- 800-FDA-1088.

What other information should I know before choosing MPA Injectable Suspension, USP?

- Pregnancy. When you take MPA Injectable Suspension, USP every 3 months, your chance of getting pregnant is very low. You could miss a period or have a light period and not be pregnant. If you miss 1 or 2 periods and think you might be pregnant, see your healthcare professional as soon as possible. You should not use MPA Injectable Suspension, USP if you are pregnant. However, MPA Injectable Suspension, USP taken by accident during pregnancy does not seem to cause birth defects.
- Nursing Mothers. Although MPA Injectable Suspension, USP can be passed to the nursing baby in the breast milk, no harmful effects on babies have been found. MPA Injectable Suspension, USP does not stop the breasts from producing milk, so it can be used by nursing mothers. However, to minimize the amount of MPA Injectable Suspension, USP that is passed to the baby in the first weeks after birth, you should wait until your baby is 6 weeks old before you start using MPA Injectable Suspension, USP for birth control.

How will MPA Injectable Suspension, USP change my periods?

- Change in normal menstrual cycle. The side effect reported most frequently by women who use MPA Injectable Suspension, USP for birth controls is a change in their normal menstrual cycle. During the first year of using MPA Injectable Suspension, USP, you might have one or more of the following changes:
  - irregular or unpredictable bleeding or spotting
  - an increase or decrease in menstrual bleeding
  - no bleeding at all. In clinical studies of MPA Injectable Suspension, USP, 55% of women reported no menstrual bleeding (amenorrhea) after one year of use and 68% of women reported no menstrual bleeding after two years of use.
- Missed period. During the time you are using MPA Injectable Suspension, USP for birth controls, you may skip a period, or your periods may stop completely. If you have been receiving your shot of MPA Injectable Suspension, USP regularly every 3 months, then you are probably not pregnant. However, if you think that you may be pregnant, see your healthcare professional.

Unusually heavy or continuous bleeding is not a usual effect of MPA Injectable Suspension, USP and if this happens you should see your healthcare professional right away.

With continued use of MPA Injectable Suspension, USP, bleeding usually decreases and many women stop having periods completely. When you stop using MPA Injectable Suspension, USP your menstrual period will usually, in time, return to its normal cycle.

What if I want to become pregnant?

Because MPA Injectable Suspension, USP is a long-acting birth control method, it takes some time after your last shot for its effect to wear off. Most women who try to get pregnant after using MPA Injectable Suspension, USP get pregnant within 18 months after their last shot. The length of time you use MPA Injectable Suspension, USP has no effect on how long it takes you to become pregnant after you stop using it.

General Information about MPA Injectable Suspension, USP

Medicines are sometimes prescribed for conditions that are not mentioned in patient information leaflets. This leaflet summarizes the most important information about MPA Injectable Suspension, USP. If you would like more information, talk with your healthcare professional. You can ask your healthcare professional for information about MPA Injectable Suspension, USP that is written for healthcare professionals.

What are the ingredients in MPA Injectable Suspension, USP?

Active ingredient: medroxyprogesterone acetate

Inactive ingredients: polyethylene glycol 3350, polysorbate 80, sodium chloride, methylparaben, propylparaben, and water for injection. When necessary, pH is adjusted with sodium hydroxide or hydrochloric acid, or both.

This Patient Information has been approved by the U.S. Food and Drug Administration.

Distributed by:
Prasco Laboratories
Mason, OH 45040 USA

LAB-1463-5.0

Revised: December 2025